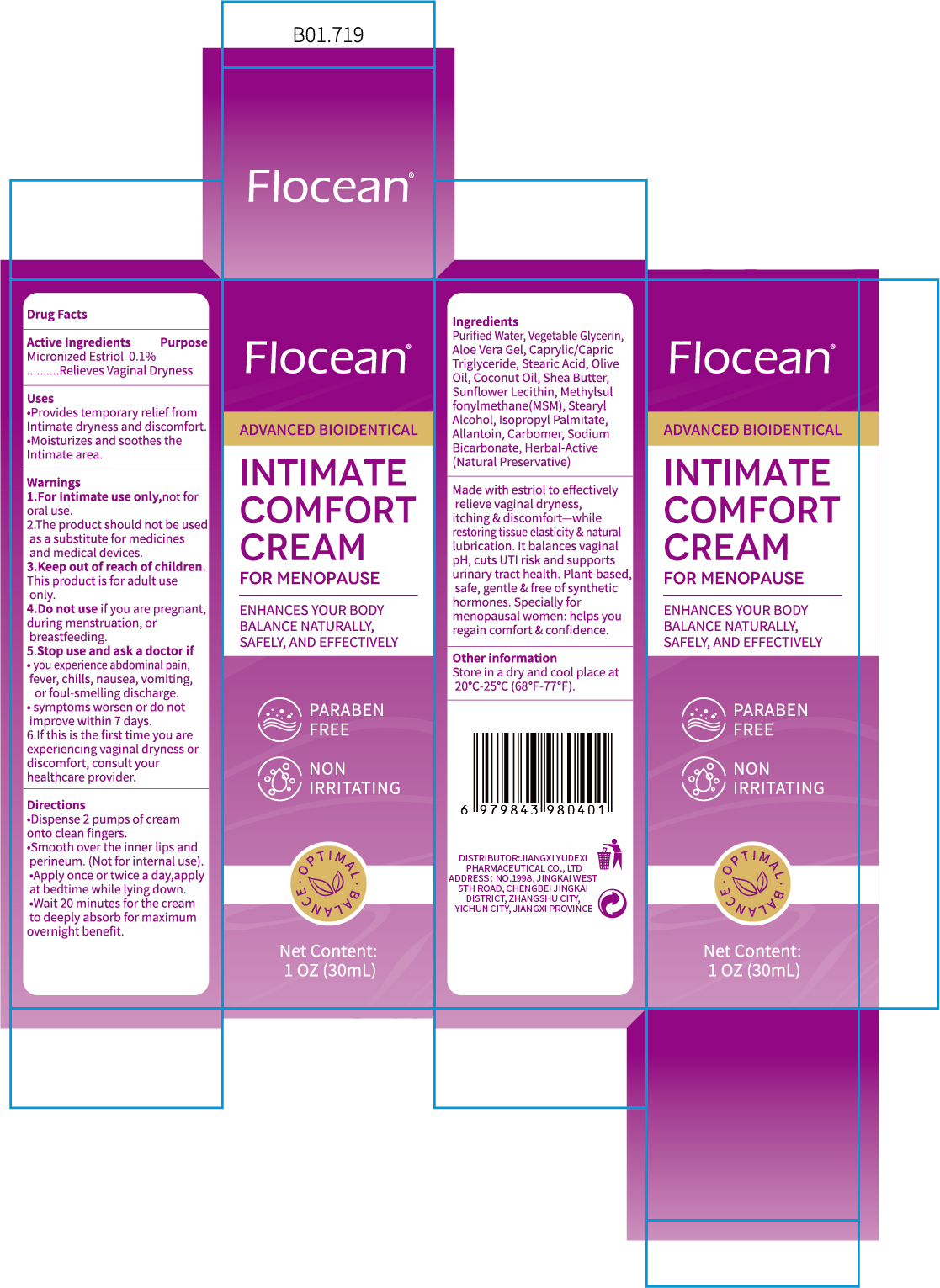 DRUG LABEL: Flocean INTIMATE COMFORT
NDC: 85248-055 | Form: CREAM
Manufacturer: Jiangxi Yudexi Pharmaceutical Co., LTD
Category: otc | Type: HUMAN OTC DRUG LABEL
Date: 20260206

ACTIVE INGREDIENTS: ESTRIOL 0.1 g/100 mL
INACTIVE INGREDIENTS: ISOPROPYL PALMITATE; CARBOMER; ALLANTOIN; GLYCERIN; STEARYL ALCOHOL; ALOE VERA LEAF; LECITHIN, SUNFLOWER; SHEA BUTTER; OLIVE OIL; COCONUT OIL; SODIUM BICARBONATE; DIMETHYL SULFONE; STEARIC ACID; CAPRYLIC/CAPRIC TRIGLYCERIDE; WATER

85248-055

Active Ingredient

Micronized Estriol 0.1%

Purpose

Relieves Vaginal Dryness

Use

·Provides temporary relief from Intimate dryness and discomfort.
·Moisturizes and soothes the Intimate area.

Warnings

1.For lntimate use only,not for oral use.

2.The product should not be used as a substitute for medicines and medical devices.

Do not use if you are pregnant,during menstruation, or breastfeeding.

When Using

lf this is the first time you are experiencing vaginal dryness or discomfort. consult your healthcare provider.

Stop Use

·you experience abdominal pain,fever, chills,nausea.vomiting, of foul-smelling discharge.
·symptoms worsen or do not improve within 7 days.

Ask Doctor

·you experience abdominal pain.fever, chills, nausea, vomiting or foul-smelling discharge.
·symptoms worsen or do not improve within 7 days.

Keep Oot Of Reach Of Children

This product is for adult use onlv.

Directions

·Dispense 2 pumps of cream onto clean fingers. ·Smooth over the inner lips and perineum.(Not for internal use). ·Apply once or twice a day, apply at bedtime while lying down.
·Wait 20 minutes for the cream to deeply absorb for maximum overnight benefit.

Other information

Store in a dry and cool place at 20°C-25°C(68°F-77°F).

Inactive ingredients

Purified Water, Vegetable Glycerin, Aloe Vera Gel.Caprylic/Capric Triglyceride.Stearic Acid， Olive Oil.Coconut Oil.Shea Butter, Sunflower Lecithin，Methylsulfonylmethane(MsM).Stearyl Alcohol,Isopropyl Palmitate,Allantoin.Carbomer, Sodium Bicarbonate, Herbal-Active （Natural Preservative)